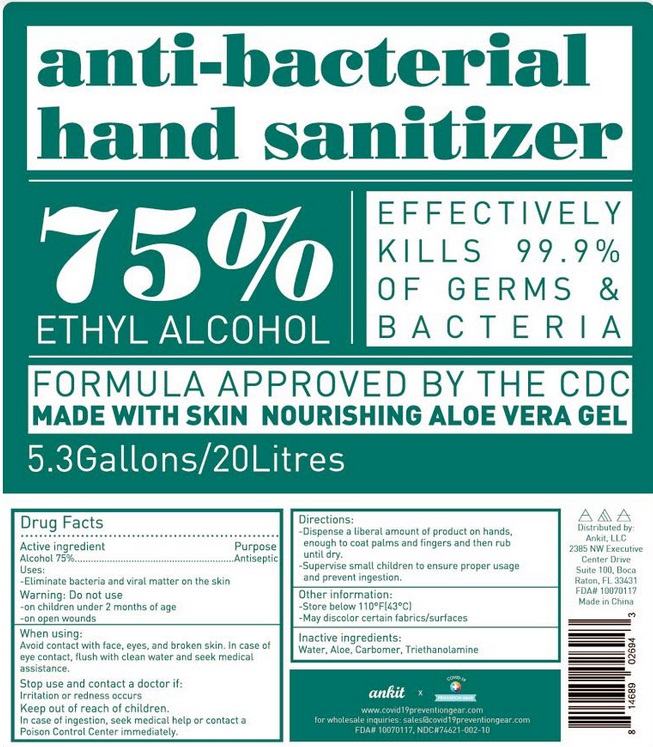 DRUG LABEL: Antibacterial hand sanitizer
NDC: 78887-001 | Form: LIQUID
Manufacturer: Ankit LLC
Category: otc | Type: HUMAN OTC DRUG LABEL
Date: 20200614

ACTIVE INGREDIENTS: ALCOHOL 75 mL/100 mL
INACTIVE INGREDIENTS: WATER; ALOE VERA LEAF; CARBOMER HOMOPOLYMER, UNSPECIFIED TYPE; TROLAMINE

Active Ingredient

Alcohol 75% v/v.

Purpose

Antiseptic

Uses

Eliminate bacteria and viral matter on the skin.

Warnings

Do not use

- on children under 2 months of age
- on open wounds

When using:

Avoid contact with face. eyes. and broken skin. In case of eye contact, flush with clean water and seek medical assistance.

Stop use and contact a doctor if:
Irritation or redness occurs.

Keep out of reach of children. In case of ingestion. seek medical help or contact a Poison Control Center immediately.

Directions

- Dispense a liberal amount of product on hands, enough to coat palms and fingers and then rub until dry.
- Supervise small children to ensure proper usage and prevent ingestion.

Other information

- Store below 110°F[43°C].
- May discolor certain fabrics/surfaces.

Inactive ingredients

Water, Aloe, Carbomer, Triethanolamine.